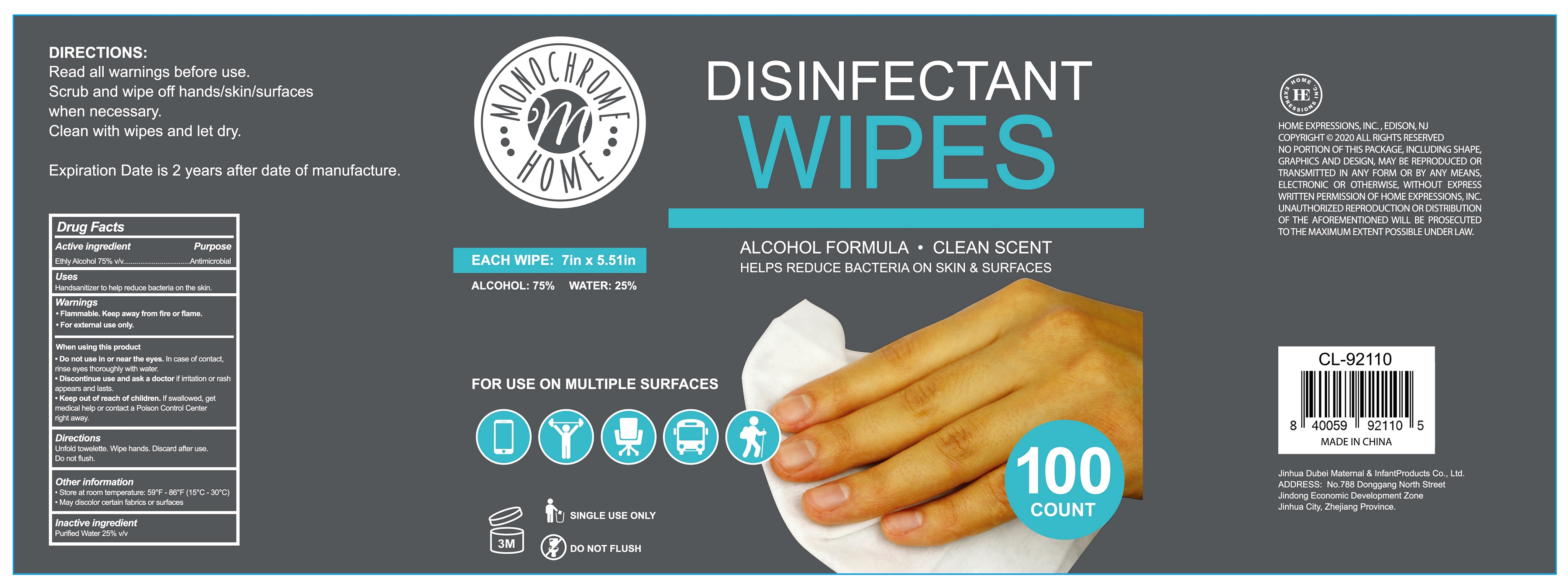 DRUG LABEL: DISINFECTANT WIPES
NDC: 41382-100 | Form: CLOTH
Manufacturer: Jinhua Dubei Maternal & Infant Products Co., Ltd.
Category: otc | Type: HUMAN OTC DRUG LABEL
Date: 20200904

ACTIVE INGREDIENTS: ALCOHOL 75 mL/100 1
INACTIVE INGREDIENTS: WATER

41382-100 DISINFECTANT WIPES

Active Ingredient(s)

Ethyl Alcohol 75% v/v. Purpose: Antimicrobial

Purpose

Antimicrobial,DISINFECTANT WIPES

Use

Handsanitizer to help reduce bacteria on the skin.

Warnings

- Flammable, Keep away from fire or flame.
- For external use only.

- Do not use in or near the eyes. In case of contact, rinse eyes thoroughly with water.

When using this product

- Do not use in or near the eyes. In case of contact, rinse eyes thoroughly with water.
- Discontinue use and ask a doctor if irritation or rash appears and lasts.
- Keep out of reach of children. If swallowed, get medical help or contact a Poison Control Center right away.

STOP USE

Discontinue use and ask a doctor if irritation or rash appears and lasts.

Keep out of reach of children. If swallowed, get medical help or contact a Poison Control Center right away.

Directions

Unfold towelette. Wipe hands. Discard after use. Do not flush.

Other information

- Store at room temperature:59℉ - 86℉（15℃ - 30℃)
- May discolor certain fabrics or surfaces

Inactive ingredients

purified water USP

Package Label - Principal Display Panel

100 cloth in 1 bag ndc:41382-100-01